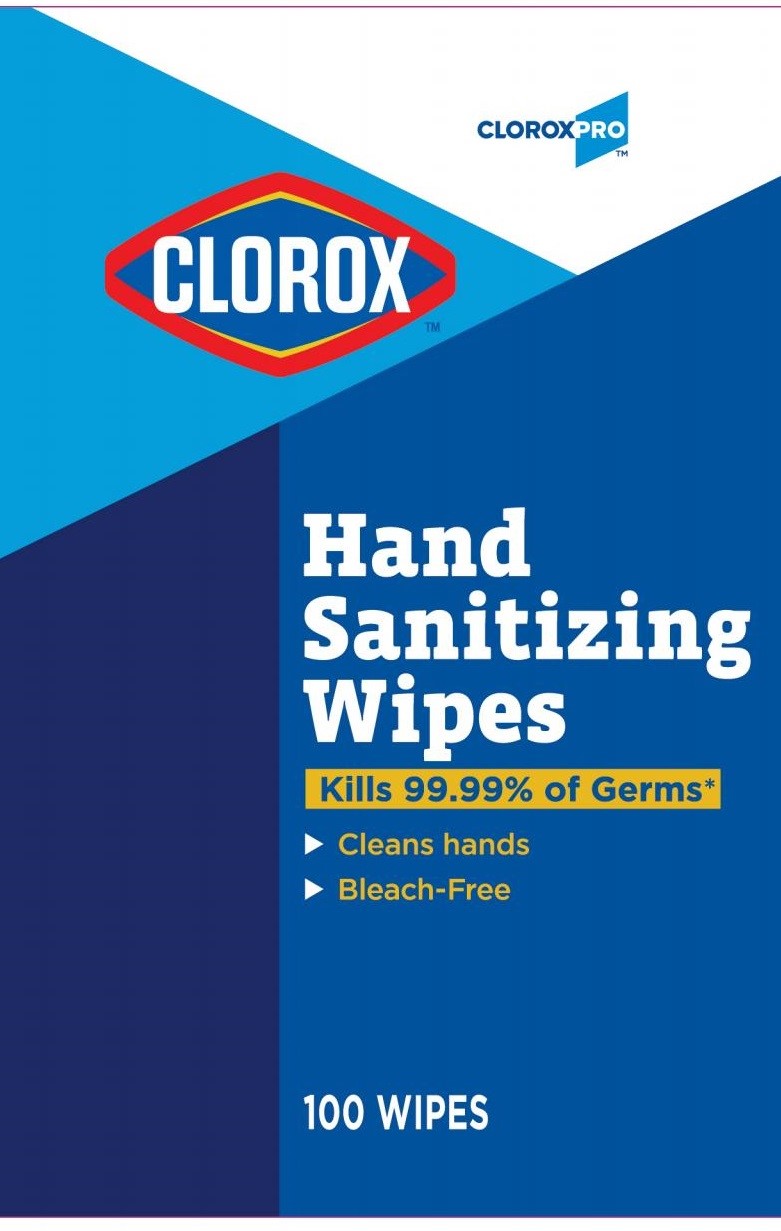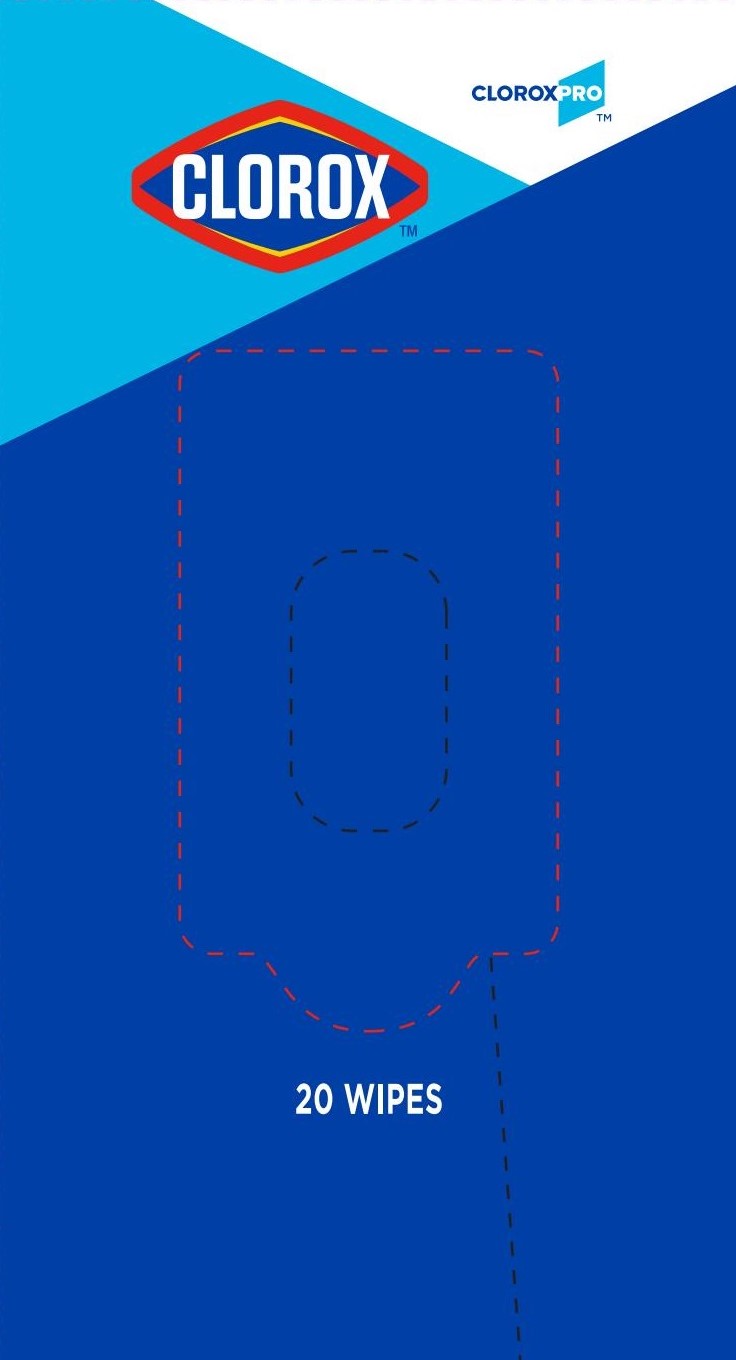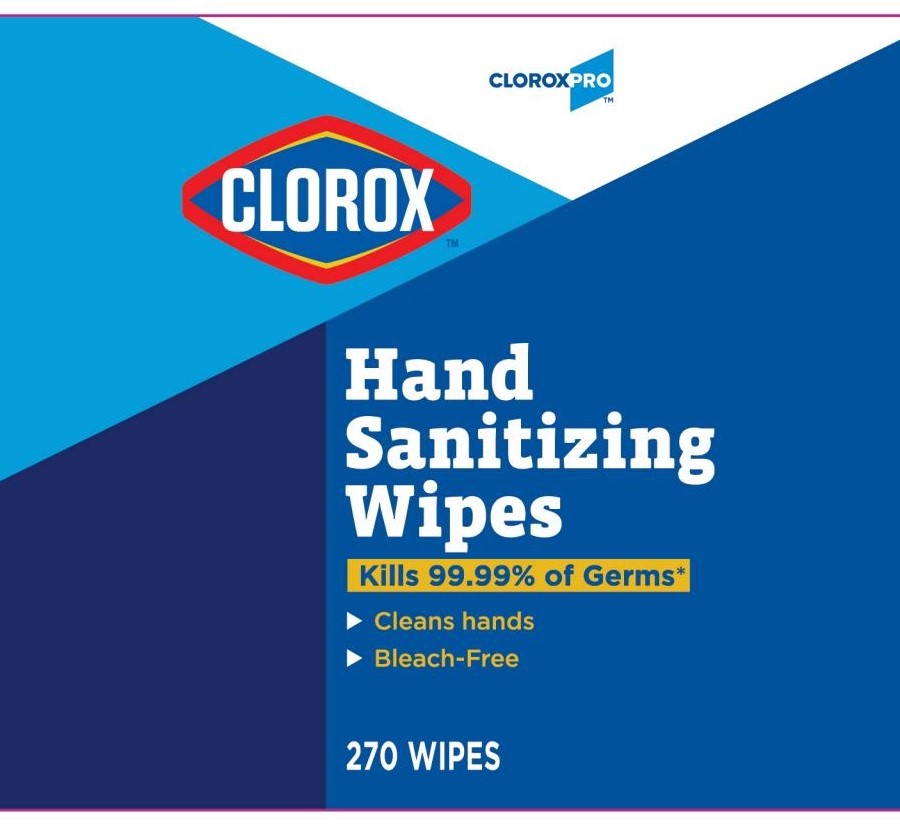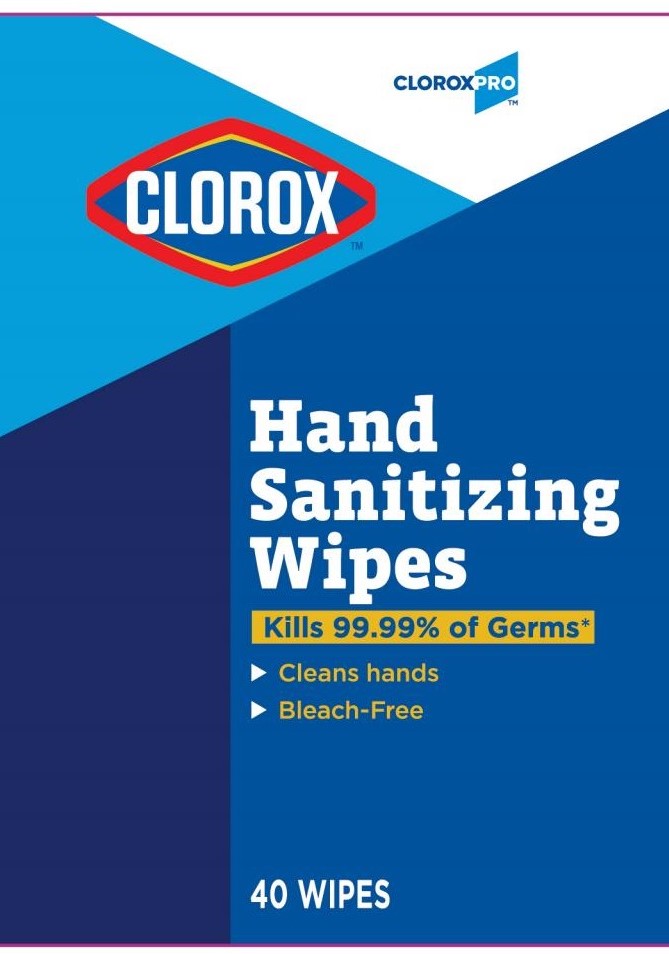 DRUG LABEL: Clorox Hand Sanitizer
NDC: 69540-0036 | Form: CLOTH
Manufacturer: Brand Buzz LLC
Category: otc | Type: HUMAN OTC DRUG LABEL
Date: 20250303

ACTIVE INGREDIENTS: BENZALKONIUM CHLORIDE 0.13 g/100 g
INACTIVE INGREDIENTS: ALOE VERA LEAF; PEG-75 LANOLIN; QUATERNIUM-52; PEG-8 DIMETHICONE; DISODIUM COCOAMPHODIACETATE; MATRICARIA CHAMOMILLA FLOWERING TOP; PHENOXYETHANOL; POTASSIUM SORBATE; CETYLPYRIDINIUM CHLORIDE; SODIUM BENZOATE; CITRIC ACID MONOHYDRATE; WATER

Clorox Pro Hand Sanitizing Wipes

Active ingredient

Benzalkonium Chloride 0.13%

Purpose

Antimicrobial

Uses

- Hand sanitizing to help reduce bacteria on the skin.

Warnings

For external use only.

When using this product

- Do not use in or near the eyes. In case of contact, rinse eyes thoroughly with water.
- Discontinue use if irritation and redness develop. If condition persists for more than 72 hours, consult a physician.

Keep out of reach of children.

If swallowed, get medical help or contact a Poison Control Center right away

Directions

- Wet hands thoroughly with product and allow to dry.

Inactive ingredients

Water, Disodium Cocoamphodiacetate, Phenoxyethanol, Aloe, Barbadensis Leaf Juice, Chamomile Flower Extract, Sodium Benzoate, Potassium Sorbate, Quaternium-52, PEG-75 Lanolin, PEG-8 Dimethicone, Dosodium EDTA, Citric Acid, Cetylpyridium Chloride

Questions of Comments?

Visit us at www.brandbuzzcp.com or call us at 1-888-508-4750

PACKAGE LABEL

CLOROX PRO™

CLOROX™

Hand Sanitizing Wipes

Kills 99.99% Germs*

- Cleans hands
- Bleach-Free

CloroxPro™ Hand Sanitizing Wipes kill 99.99% of mopst illness causing germs, so you can clean your hands with confidence.

*kills 99.99% of most illness causing germs

Wipe dimensions: 5.75in. x 7.5in. (14.6 cm x 19 cm)

1. Remove lid by lifting upward.
2. Pull wipe from center of the roll and thread through the underside of lid. DO NOT put finger through the hole.
3. Close lid and pull wipe from canister at an angle.
4. Snap lid cap shut to retain moisture.

To Dispose: Place in waste basket after use. DO NOT FLUSH

Developed in USA | Responsibly Made in China ©2021

Distributed by Brand Buzz LLC., 1407 Broadway, NEw York, NY 10018

CLOROX and other trademarks are used by Brand Buzz LLC under license from The Clorox Company or its affiliates.

20 WIPES

40 WIPES

100 WIPES

270 WIPES